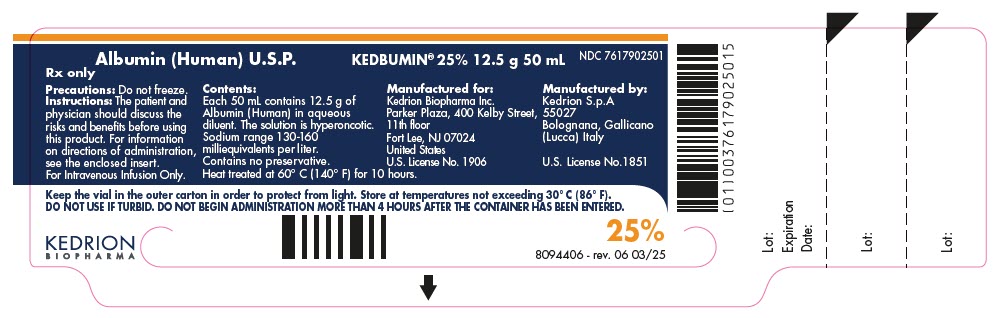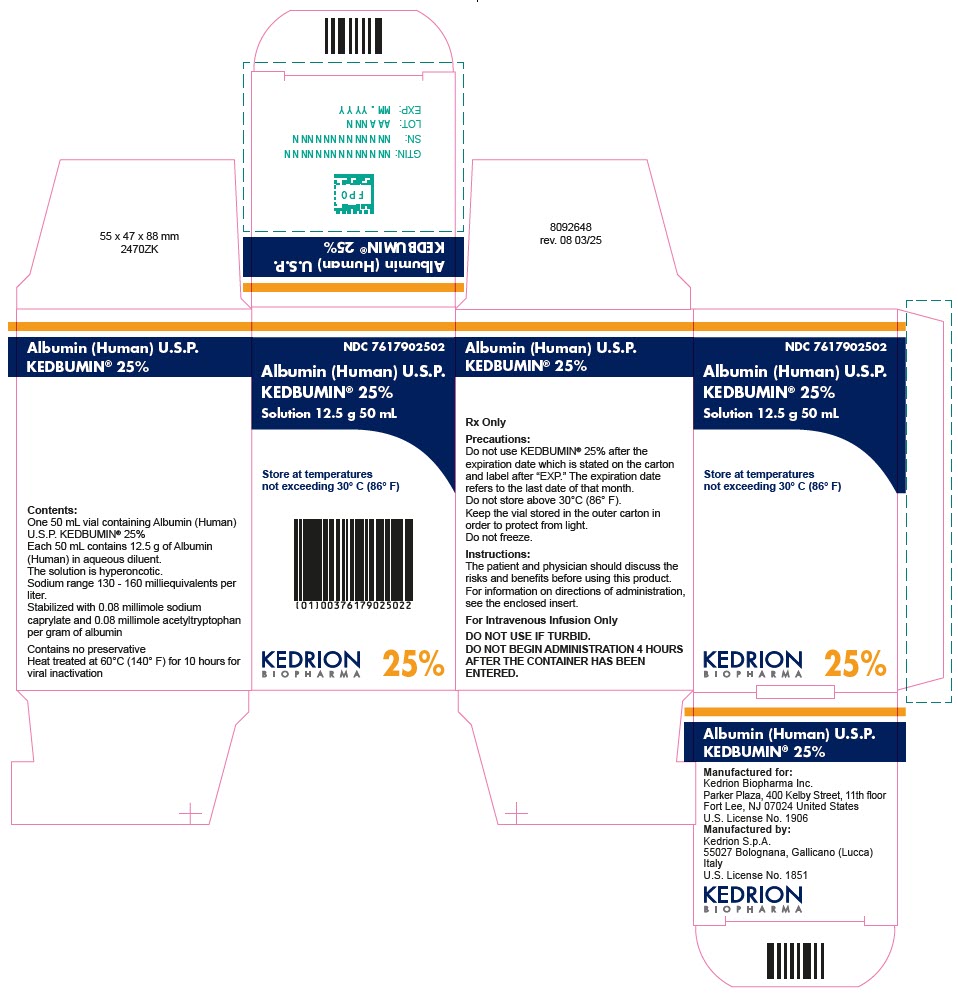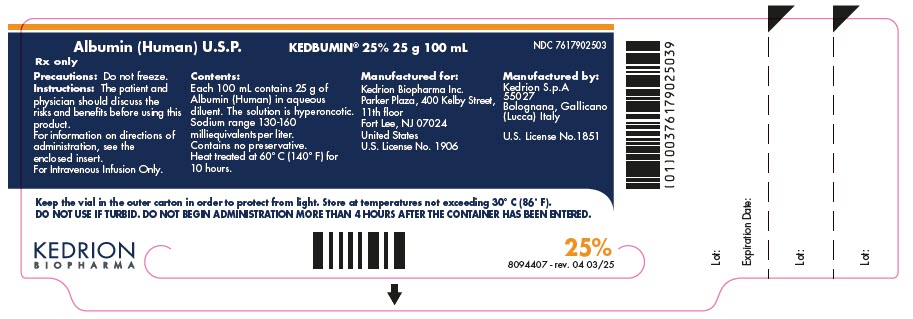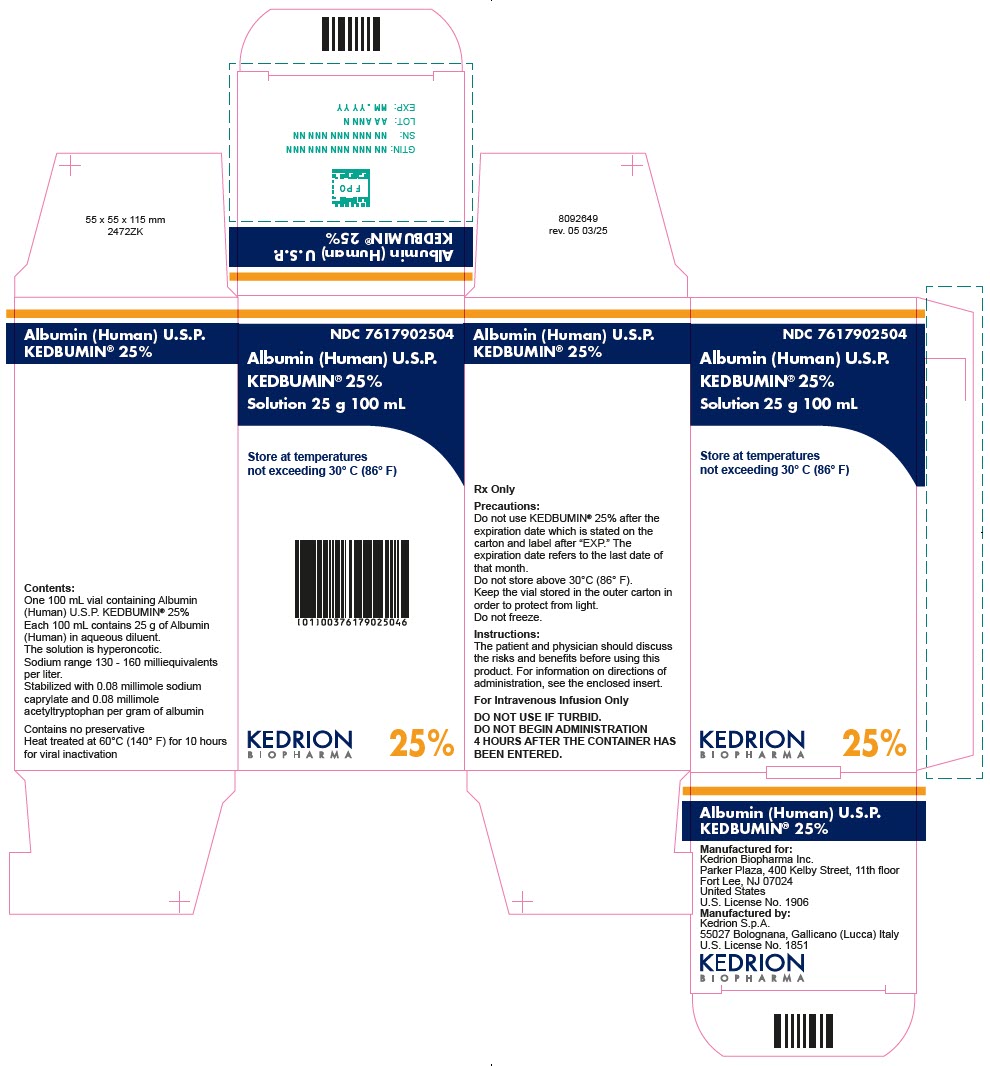 DRUG LABEL: KEDBUMIN
NDC: 76179-025 | Form: INJECTION, SOLUTION
Manufacturer: Kedrion S.p.A
Category: other | Type: PLASMA DERIVATIVE
Date: 20250627

ACTIVE INGREDIENTS: ALBUMIN HUMAN 12.5 g/50 mL

HIGHLIGHTS OF PRESCRIBING INFORMATION

These highlights do not include all the information needed to use KEDBUMIN® safely and effectively. See full prescribing information for KEDBUMIN® [Albumin (Human) U.S.P.] sterile, aqueous solution for single dose intravenous administration
Initial U.S. Approval: June, 2011.

1. INDICATIONS AND USAGE

KEDBUMIN® is a 25% albumin solution indicated for:

- Hypovolemia (1.1) and Hypoalbuminemia (1.2)
- Prevention of central volume depletion after paracentesis due to cirrhotic ascites (1.3)
- Ovarian hyperstimulation syndrome (OHSS) (1.4)
- Adult Respiratory Distress Syndrome (ARDS) (1.5)
- Burns (1.6)
- Hemodialysis patients undergoing long term dialysis (1.7)
- Patients who cannot tolerate substantial volumes of salt solution (1.7)
- Priming as part of a cardiopulmonary bypass fluids (1.8)

2. DOSAGE AND ADMINISTRATION

Intravenous Administration Only. KEDBUMIN® may be diluted with 5% glucose or 0.9% sodium chloride. Concentration, dosage, and infusion-rate should be adjusted to the patient's individual requirements and indication (2.1). Daily dosage should not exceed 2g per kg body weight.

Indication: Dose
Hypovolemia: | Adults: Initial dose 25 g is suggested.
Hypoalbuminemia: | 50-75 g
Prevention of Central Volume Depletion after Paracentesis due to Cirrhotic Ascites: | Adults: 6-8 g for every 1000 mL of ascitic fluid removed
OHSS: | Adults: 50 to 100 g over 4 hours and repeated at 4-12 hour intervals as necessary. 10-50 g; single infusion
ARDS: | Adults: 25 g over 30 minutes and repeated at 8 hours for 3 days if necessary
Burns: | Determined by direct observation of vital sign or measurement of either plasma oncotic pressure or protein content
Hemodialysis: | 100 mL
Cardiopulmonary Bypass: | Estimated from the difference between the desired and actual total serum protein concentration times the estimated plasma volume (approx 40mL per kg) times 2

3. DOSAGE FORMS AND STRENGTHS

KEDBUMIN® is a sterile, single dose solution containing 0.25 g per mL human albumin in the following presentation:

- 12.5 g albumin per 50 mL single dose vial (3)
- 25 g albumin per 100 mL single dose vial (3)

4. CONTRAINDICATIONS

- Severe anemia or heart failure in the presence of normal or increased intravascular volume (4).
- Hypersensitivity to albumin, the excipients, or components of the container.

5. WARNINGS AND PRECAUTIONS

- Risk of transmission of infectious agents (5.1).
- Caution where hypervolemia and its consequences or hemodilution could represent a special risk (5.2)
- Do not dilute with water for injection (5.2)

6. ADVERSE REACTIONS

The most common adverse reactions include fever, chills, rash, nausea, vomiting, tachycardia, and hypotension (6).

To report SUSPECTED ADVERSE REACTIONS, contact Kedrion Biopharma, Inc. at 1-855-3KDRION (1-855-353-7466) or the FDA at 1-800-FDA-1088 or www.fda.gov/medwatch

8. USE IN SPECIFIC POPULATIONS

Pediatric use: ages 12-16 years use as in adults (8.4)

FULL PRESCRIBING INFORMATION

1. INDICATIONS AND USAGE

1.1 Hypovolemia

For restoration and maintenance of circulating blood volume where volume deficiency is demonstrated and colloid use is appropriate.

1.2 Hypoalbuminemia

KEDBUMIN® is indicated for severe albumin deficiency caused by illness or active bleeding. When albumin deficiency results from excessive protein loss, the effect of albumin administration will be temporary unless the underlying disorder is reversed.

1.3 Prevention of Central Volume Depletion after Paracentesis due to Cirrhotic Ascites

KEDBUMIN® is indicated for maintenance of cardiovascular function following the removal of large volumes of ascitic fluid due to cirrhosis [1, 2].

1.4 Ovarian Hyperstimulation Syndrome (OHSS)

KEDBUMIN® is indicated as a plasma expander in the fluid management of severe forms of ovarian hyperstimulation syndrome (OHSS) [3, 4].

1.5 Adult Respiratory Distress Syndrome (ARDS)

KEDBUMIN® is indicated in conjunction with diuretics to correct fluid volume overload associated with ARDS [5].

1.6 Burns

KEDBUMIN® is indicated after > 24 hours post burn in patients experiencing severe albumin depletion in order to favor edema re-absorption [6].

1.7 Hemodialysis

KEDBUMIN® is indicated in patients undergoing long term dialysis or for those patients who are fluid-overloaded and cannot tolerate substantial volumes of salt solution for therapy of shock or hypotension [7].

1.8 Cardiopulmonary Bypass

KEDBUMIN® is indicated in cardiopulmonary bypass procedures as part of the priming fluids [8, 9].

2. DOSAGE AND ADMINISTRATION

Intravenous Administration Only.

2.1 Dosage

The concentration of the albumin preparation, dosage, and infusion-rate should be adjusted to the patient's individual requirements and indication.

Indication | Dose
Hypovolemia | Adults: Initial dose of 25 g is suggested. Pediatric dosage should be adjusted based upon on age, weight and clinical conditions
Hypoalbuminemia | 50-75 g
Prevention of Central Volume Depletion after Paracentesis due to Cirrhotic Ascites | Adults: 6-8 g for every 1000 mL of ascitic fluid removed
OHSS | Adults: 50-100 g over 4 hours and repeated at 4-12 hour intervals as necessary. 10-50 g: single infusion
ARDS | Adults: 25 g over 30 minutes and repeated at 8 hours for 3 days if necessary
Burns | The amount of albumin required to achieve adequate plasma volume and protein content should be determined by direct observation of vital signs or measurement of either plasma oncotic pressure or protein content
Hemodialysis | 100 mL
Cardiopulmonary Bypass | Required dose can be estimated from the difference between the desired and actual total serum protein concentration multiplied by the estimated plasma volume (approximately 40mL per kg) times 2 (to account for extravascular deficit, which absorbs about half of the administered dose)

2.2 Administration

Intravenous administration only.

Inspect visually for particulate matter and discoloration prior to administration, whenever the solution and container permit.

Do not dilute with sterile water for injection as hemolysis may occur (5.3).

KEDBUMIN® may be diluted with 5% glucose or 0.9% sodium chloride.

Adjust the infusion rate to the rate of removal in plasma exchange.

Warm the product to room temperature if large volumes are to be administered.

Do not begin administration > 4 hours after the container has been entered. Discard unused material.

Record the batch number every time KEDBUMIN® is administered to a patient.

3. DOSAGE FORMS AND STRENGTHS

KEDBUMIN® is a sterile, aqueous solution for single dose administration intravenously. The product contains 0.25 g per mL human albumin and is available in the following presentation [10]:

- 12.5 g albumin per 50 mL single dose vial
- 25.0 g albumin per 100 mL single dose vial

4. CONTRAINDICATIONS

KEDBUMIN® is contraindicated in patients with a history of hypersensitivity to albumin, excipients used in its formulation, or components of the container [11].

KEDBUMIN® is also contraindicated in severely anemic patients and in patients with heart failure.

5. WARNINGS AND PRECAUTIONS

5.1 Hypersensitivity

Hypersensitivity or allergic reactions have been observed, and may in some cases progress to severe anaphylaxis. Epinephrine should be available immediately to treat any acute hypersensitivity reaction.

5.2 Hypervolemia

KEDBUMIN® should be used with caution in conditions where hypervolemia and its consequences or hemodilution could represent a special risk (10). Examples of such conditions may include but are not limited to:

- Heart failure
- Arterial hypertension
- Esophageal varices
- Pulmonary edema
- Hemorrhagic diathesis
- Severe anemia
- Renal and post-renal anuria

5.3 Hemolysis

Do not dilute KEDBUMIN® with Sterile Water for Injection, as this may cause hemolysis in recipients. There is a risk of potentially fatal hemolysis and acute renal failure from the use of Sterile Water for Injection as a diluent for 25% albumin ^12. Suitable solutions for dilution include 5% glucose and 0.9% sodium chloride (2.2).

5.4 Large Volumes

When replacing comparatively large volumes of albumin, control of coagulation and hematocrit is essential. Ensure adequate substitution of other blood constituents as coagulation factors, electrolytes, platelets, and erythrocytes.

5.5 Hydration

The colloid osmotic effect of KEDBUMIN® 25% is approximately four times that of human blood. Therefore, when concentrated albumin is administered, ensure adequate hydration of the patient. Carefully monitor to guard against circulatory overload (10).

Hemodynamic performance should be monitored regularly. This may include arterial blood pressure and pulse rate, central venous pressure, pulmonary artery occlusion pressure, urine output, electrolyte levels, and hematocrit/hemoglobin.

5.6 Infectious Diseases

Albumin is a derivative of human blood. Based on effective donor screening and product manufacturing processes, it carries an extremely remote risk for transmission of viral diseases and variant Creutzfeldt-Jakob disease (vCJD). There is a theoretical risk for transmission of Creutzfeldt-Jakob disease (CJD), but if that risk actually exists, the risk of transmission would also be considered extremely remote. No cases of transmission of viral diseases, CJD or vCJD have ever been identified for licensed albumin.

ALL infections suspected by a physician possibly to have been transmitted by this product should be reported by the physician or other healthcare provider to Kedrion Biopharma, Inc. at 1-855-3KDRION (1-855-353-7466).

See also PATIENT COUNSELING INFORMATION (17).

6. ADVERSE REACTIONS

6.1 General

The most common adverse reactions include flushing, urticaria, fever, chills, nausea, vomiting, tachycardia and hypotension. These reactions normally disappear when the infusion rate is slowed or stopped.

If a severe reaction such as shock or anaphylaxis occurs, the infusion should be stopped and appropriate treatment initiated.

7. DRUG INTERACTION

KEDBUMIN® should not be mixed with other medicinal products including blood and blood components, but can be administered concomitantly with other parenterals such as whole blood, plasma, saline, glucose or sodium lactate when medically necessary.

KEDBUMIN® should not be mixed with protein hydrolysates or solutions containing alcohol since these combinations may cause protein precipitation.

8. USE IN SPECIFIC POPULATIONS

8.1 Pregnancy

Risk Summary

No human or animal data are available to indicate the presence or absence of drug-associated risk. It is not known whether KEDBUMIN® can cause fetal harm when administered to a pregnant woman or can affect reproductive capacity.

8.2 Lactation

Risk Summary

No human or animal data are available to indicate the presence or absence of drug-associated risk. It is not known whether KEDBUMIN® is excreted in milk.

8.4 Pediatric Use

The adult dose may be given in children 12-16 years of age. Use of KEDBUMIN® in children less than 12 years of age has not been clinically evaluated. If administered to children the dosage will vary with the clinical state and body weight of the individual. Typically, a dose one-fourth to one-half the adult dose may be administered. The usual rate of administration in children should be one-fourth the adult rate. Physicians should weigh the risks and benefits of KEDBUMIN® in the pediatric population.

10. OVERDOSE

Hypervolemia may occur if the dosage and rate of infusion are too high. At the first clinical sign of circulatory overload, e.g. headache, dyspnea, jugular venous congestion, increased blood pressure, raised central venous pressure, or pulmonary edema, the infusion should be stopped and hemodynamic parameters carefully monitored. Additionally, diuresis or cardiac output should be increased in accordance with the severity of the clinical situation (5.2).

11. DESCRIPTION

KEDBUMIN® is a sterile, aqueous solution for single dose intravenous administration. The product contains 0.25 g per mL human albumin and is prepared by cold ethanol fractionation from pooled human plasma obtained from venous blood at FDA-licensed facilities located in the USA. Intermediate source material (Fraction V paste) is obtained from a U.S. licensed manufacturer. The colloid osmotic effect of KEDBUMIN® is approximately four times that of blood plasma.

KEDBUMIN® is a clear, slightly viscous liquid, with a yellow, amber, or green tint. The product is stabilized by the addition of 0.08 mmol sodium caprylate and 0.08 mmol sodium acetyltryptophan per gram of albumin. Additionally, each liter of material contains 130-160 mEq of sodium ion and ≤ 200 μg of aluminum. The product contains no preservatives.

KEDBUMIN® is heated for ten hours at 60 °C (140°F). The KEDBUMIN® manufacturing process results in viral reduction in in vitro studies (see table below). These reductions are achieved through a combination of process steps including Cohn fractionation and final container heat treatment.

 | Mean Reduction Factor (log10)
 | Enveloped viruses |  |  | Non-enveloped viruses
Manufacturing Step | HIV-1 | BVDV | PRV | REO | PPV | HAV | EMCV
Precipitation of Fraction II +III | 3.4 | 3.5 | 3.9
Precipitation of Fraction IV-1 and Precipitation of Fraction IV-4 |  |  |  | > 7.11 | 3.44 | > 5.72 | 5.97
Ethanol inactivation during Fraction V precipitation | > 3.71 | > 5.68 | > 3.38
Heat treatment (Pasteurization) | > 5.40 | > 5.11 | > 6.90 | 6.88 | 2.00 [scientific data suggest that the actual human parvovirus B19 (B19V) is far more effectively inactivated by pasteurization than indicated by model virus data [15, 16].] | 3.94
Overall Virus Reduction Factor | >12.51 | >14.29 | >14.18 | >13.99 | 5.44 | > 9.66 | 5.97
HIV-1: Human Immunodeficiency Virus Type 1
BVDV: Bovine Viral Diarrhoea Virus
PRV: Pseudorabies Virus
REO: Reovirus
PPV: Porcine Parvovirus
HAV: Hepatitis A Virus
EMCV: Encephalomyocarditis Virus

12. CLINICAL PHARMACOLOGY

12.1 Mechanism of Action

Human albumin is not a glycoprotein. It has the lowest molecular weight (66,241 Daltons) of all plasma proteins. Because of its three dimensional structure, solutions of albumin have a lower viscosity than solutions of other plasma proteins. This is important since work performed by the heart depends in part on the viscosity of blood. Human albumin accounts quantitatively for more than half of the total proteins in the circulation (by weight) and represents approximately 10 % of the protein synthesized in the liver.

Approximately 40% of albumin is contained in the circulation. The remainder is located in the extravascular space of tissues, principally muscle, skin, and intestine.

KEDBUMIN® 25% has a hyperoncotic effect.

A major function of albumin is its role in osmotic regulation. Albumin is responsible for 75% of normal oncotic pressure within the intravascular space [13, 14]. Other physiological functions include binding and transport of molecules (hormones, enzymes, drugs and toxins); free radical scavenging; hemostatic effects (platelet function inhibition and antithrombotic effects); and capillary membrane permeability [14].

12.3 Pharmacokinetics

Under normal conditions, the total exchangeable albumin pool is 4-5 g per kg body weight, of which 40-45% is present intravascularly and 55-60% is in the extravascular space. Increased capillary permeability will alter albumin kinetics and abnormal distribution may occur in conditions such as severe burns or septic shock.

Under normal conditions, the half-life of albumin is approximately 19 days. The balance between synthesis and breakdown is normally achieved by feed-back regulation. Elimination is predominantly intracellular and due to lysosomal proteases. In healthy subjects, less than 10% of infused albumin leaves the intravascular compartment during the first two hours following infusion. There is considerable individual variation in the effect on plasma volume. In some patients plasma volume can remain elevated for several hours. However, in critically ill patients, albumin can leak out of the vascular space in substantial amounts at an unpredictable rate.

15. REFERENCES

1. Vermeulen LC, Jr., Ratko TA, Erstad BL, Brecher ME, Matuszewski KA. A paradigm for consensus. The University Hospital Consortium guidelines for the use of albumin, nonprotein colloid, and crystalloid solutions. Arch Intern Med. Feb 27 1995;155(4):373-379.
2. Gines A, Fernandez-Esparrach G, Monescillo A, et al. Randomized trial comparing albumin, dextran 70, and polygeline in cirrhotic patients with ascites treated by paracentesis. Gastroenterology. Oct 1996;111(4):1002-1010.
3. Aboulghar M, Evers JH, Al-Inany H. Intravenous albumin for preventing severe ovarian hyperstimulation syndrome: a Cochrane review. Hum Reprod. Dec 2002;17(12):3027-3032.
4. Medicine PCotASfR. Ovarian Hyperstimulation Syndrome. Fertility and Sterility. 2000;86(5 Suppl 1):S178-S183. .
5. Martin GS, Moss M, Wheeler AP, Mealer M, Morris JA, Bernard GR. A randomized, controlled trial of furosemide with or without albumin in hypoproteinemic patients with acute lung injury. Crit Care Med. Aug 2005;33(8):1681-1687.
6. Manelli JC. [Is albumin administration useful in critical care for burnt patients?]. Ann Fr Anesth Reanim. 1996;15(4):507-513.
7. Tullis JL. Albumin. 2. Guidelines for clinical use. JAMA. Jan 31 1977;237(5):460-463 concl.
8. Schiff P. Albumin-containing plasma volume expanders. Aust N Z J Surg. Dec 1977;47(6):783-786.
9. Wilkes MM, Navickis RJ, Sibbald WJ. Albumin versus hydroxyethyl starch in cardiopulmonary bypass surgery: a meta-analysis of postoperative bleeding. Ann Thorac Surg. Aug 2001;72(2):527-533; discussion 534.
10. Gerety RJ, Aronson DL. Plasma derivatives and viral hepatitis. Transfusion. Sep-Oct 1982;22(5):347-351.
11. Gellis SS, Neefe JR, et al. Chemical, clinical, and immunological studies on the products of human plasma fractionation; inactivation of the virus of homologous serum hepatitis in solutions of normal human serum albumin by means of heat. J Clin Invest. Mar 1948;27(2):239-244.
12. Pierce LR, Gaines A, Finlayson JS, Varricchio F, Epstein JS. Hemolysis and acute renal failure due to the administration of albumin diluted in sterile water. Transfusion. Jan 1999;39(1):110-111.
13. Doweiko JP, Nompleggi DJ. Role of albumin in human physiology and pathophysiology. Jpen. Mar-Apr 1991;15(2):207-211.
14. Mendez CM, McClain CJ, Marsano LS. Albumin therapy in clinical practice. Nutr Clin Pract. Jun 2005;20(3):314-320.
15. Blümel J, Schmidt I, Willkommen H, Lower J. Inactivation of parvovirus B19 during pasteurization of human serum albumin. Transfusion. Aug 2002;42: 1011-1018.
16. Blümel J, Rinckel LA, Lee DC, Roth NJ, Baylis SA. Inactivation and neutralization of parvovirus B19 Genotype 3. Transfusion. Jul 2012;52:1490-1497.

16. HOW SUPPLIED/STORAGE AND HANDLING

KEDBUMIN® is supplied as a sterile, aqueous solution for single dose intravenous administration containing 0.25 g per mL human albumin. It is available in the following glass vial size:

50 mL vial 25% (NDC 76179-025-01) is packaged in one carton (NDC 76179-025-02)

100 mL vial 25% (NDC 76179-025-03) is packaged in one carton (NDC 76179-025-04)

Storage

Do not use KEDBUMIN® after the expiration date which is stated on the carton and label after "EXP." The expiration date refers to the last day of that month.

Do not store above 30°C (86° F).

Keep the vial stored in the outer carton in order to protect from light.

Do not freeze.

17. PATIENT COUNSELING INFORMATION

Inform patients being treated with KEDBUMIN® about the potential risks and benefits with its use (6). Discontinue immediately if allergic symptoms or circulatory overload occur (e.g. skin rashes, hives, itching, breathing difficulties, coughing, nausea, vomiting, fall in blood pressure, increased heart rate).

Inform patients that KEDBUMIN® is a derivative of human plasma and may contain infectious agents that cause disease (e.g., viruses, vCJD agent and, theoretically, CJD agent). Inform patients that the risk that KEDBUMIN® may transmit an infectious agent has been reduced by screening plasma donors for prior exposure for certain viruses, by testing the donated plasma for certain virus infections, and by inactivating and/or removing certain viruses during manufacturing (5).

Manufactured for:
Kedrion Biopharma Inc.
Parker Plaza, 400 Kelby Street, 11th floor
Fort Lee, NJ 07024
United States
U.S. License No. 1906

Manufactured by:
Kedrion S.p.A.
Via Provinciale Loc. Bolognana
55027 Gallicano (Lucca)
Italy
Phone: +39 0583 1969 1
Fax: +39 0583 1969 981
U.S. License No. 1851

PRINCIPAL DISPLAY PANEL - 50 mL Vial Label

Albumin (Human) U.S.P.
KEDBUMIN® 25% 12.5 g 50 mL
NDC 7617902501

Rx only

Precautions: Do not freeze.
Instructions: The patient and
physician should discuss the
risks and benefits before using
this product. For information
on directions of administration,
see the enclosed insert.
For Intravenous Infusion Only.

Contents:
Each 50 mL contains 12.5 g of
Albumin (Human) in aqueous
diluent. The solution is hyperoncotic.
Sodium range 130-160
milliequivalents per liter.
Contains no preservative.
Heat treated at 60° C (140° F) for 10 hours.

Manufactured for:
Kedrion Biopharma Inc.
Parker Plaza, 400 Kelby Street,
11th floor
Fort Lee, NJ 07024
United States
U.S. License No. 1906

Manufactured by:
Kedrion S.p.A
55027
Bolognana, Gallicano
(Lucca) Italy

U.S. License No.1851

Keep the vial in the outer carton in order to protect from light. Store at temperatures not exceeding 30° C (86° F).
DO NOT USE IF TURBID. DO NOT BEGIN ADMINISTRATION MORE THAN 4 HOURS AFTER THE CONTAINER HAS BEEN ENTERED.

KEDRION
BIOPHARMA

25%
8094406 - rev. 06 03/25

PRINCIPAL DISPLAY PANEL - 50 mL Vial Carton

NDC 7617902502

Albumin (Human) U.S.P.
KEDBUMIN® 25%
Solution 12.5 g 50 mL

Store at temperatures
not exceeding 30° C (86° F)

KEDRION
BIOPHARMA
25%

PRINCIPAL DISPLAY PANEL - 100 mL Vial Label

Albumin (Human) U.S.P.
KEDBUMIN® 25% 25 g 100 mL
NDC 7617902503

Rx only

Precautions: Do not freeze.
Instructions: The patient and
physician should discuss the
risks and benefits before using this
product.
For information on directions of
administration, see the
enclosed insert.
For Intravenous Infusion Only.

Contents:
Each 100 mL contains 25 g of
Albumin (Human) in aqueous
diluent. The solution is hyperoncotic.
Sodium range 130-160
milliequivalents per liter.
Contains no preservative.
Heat treated at 60° C (140° F) for
10 hours.

Manufactured for:
Kedrion Biopharma Inc.
Parker Plaza, 400 Kelby Street,
11th floor
Fort Lee, NJ 07024
United States
U.S. License No. 1906

Manufactured by:
Kedrion S.p.A
55027
Bolognana, Gallicano
(Lucca) Italy

U.S. License No.1851

Keep the vial in the outer carton in order to protect from light. Store at temperatures not exceeding 30° C (86° F).
DO NOT USE IF TURBID. DO NOT BEGIN ADMINISTRATION MORE THAN 4 HOURS AFTER THE CONTAINER HAS BEEN ENTERED.

KEDRION
BIOPHARMA

25%
8094407 - rev. 04 03/25

PRINCIPAL DISPLAY PANEL - 100 mL Vial Carton

NDC 7617902504

Albumin (Human) U.S.P.
KEDBUMIN® 25%
Solution 25 g 100 mL

Store at temperatures
not exceeding 30° C (86° F)

KEDRION
BIOPHARMA

25%